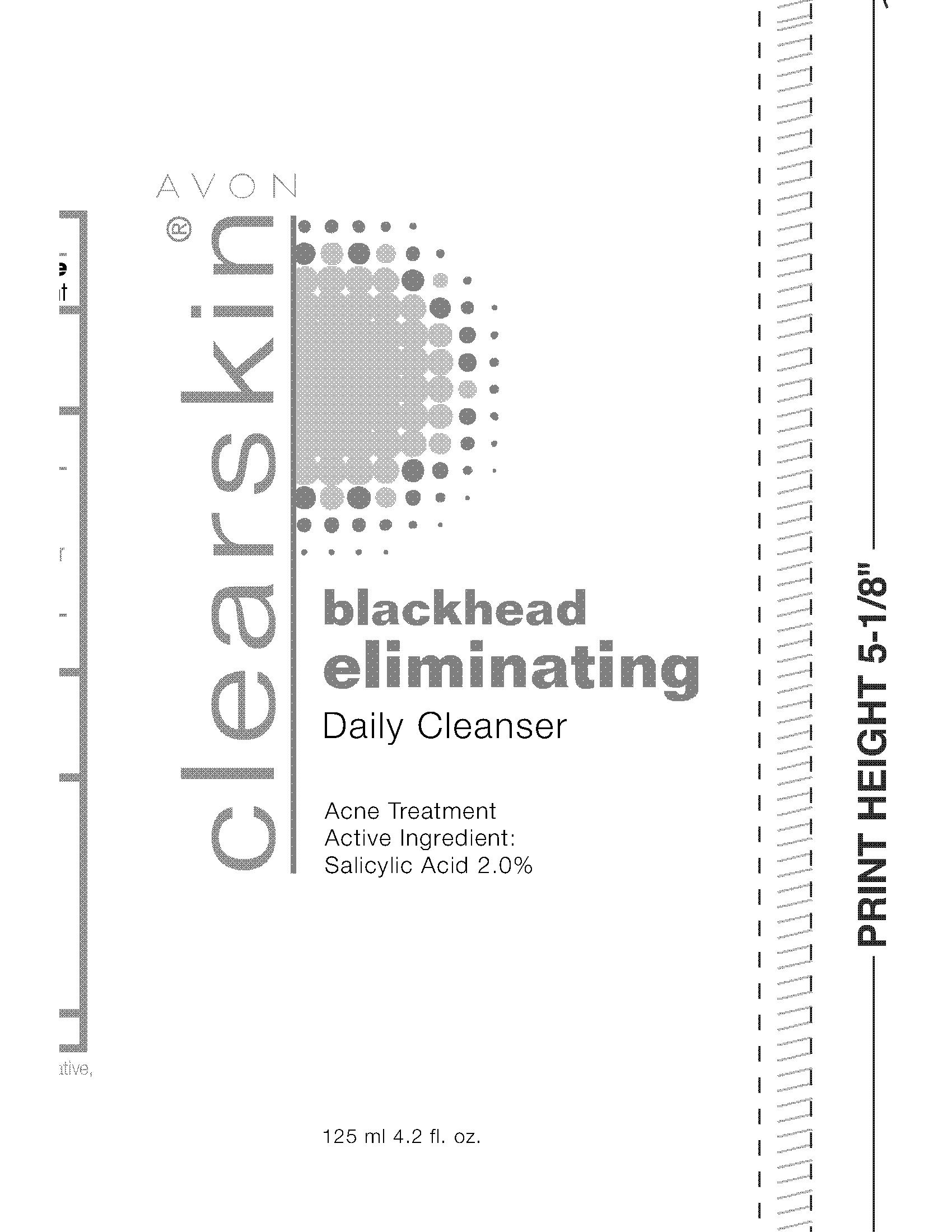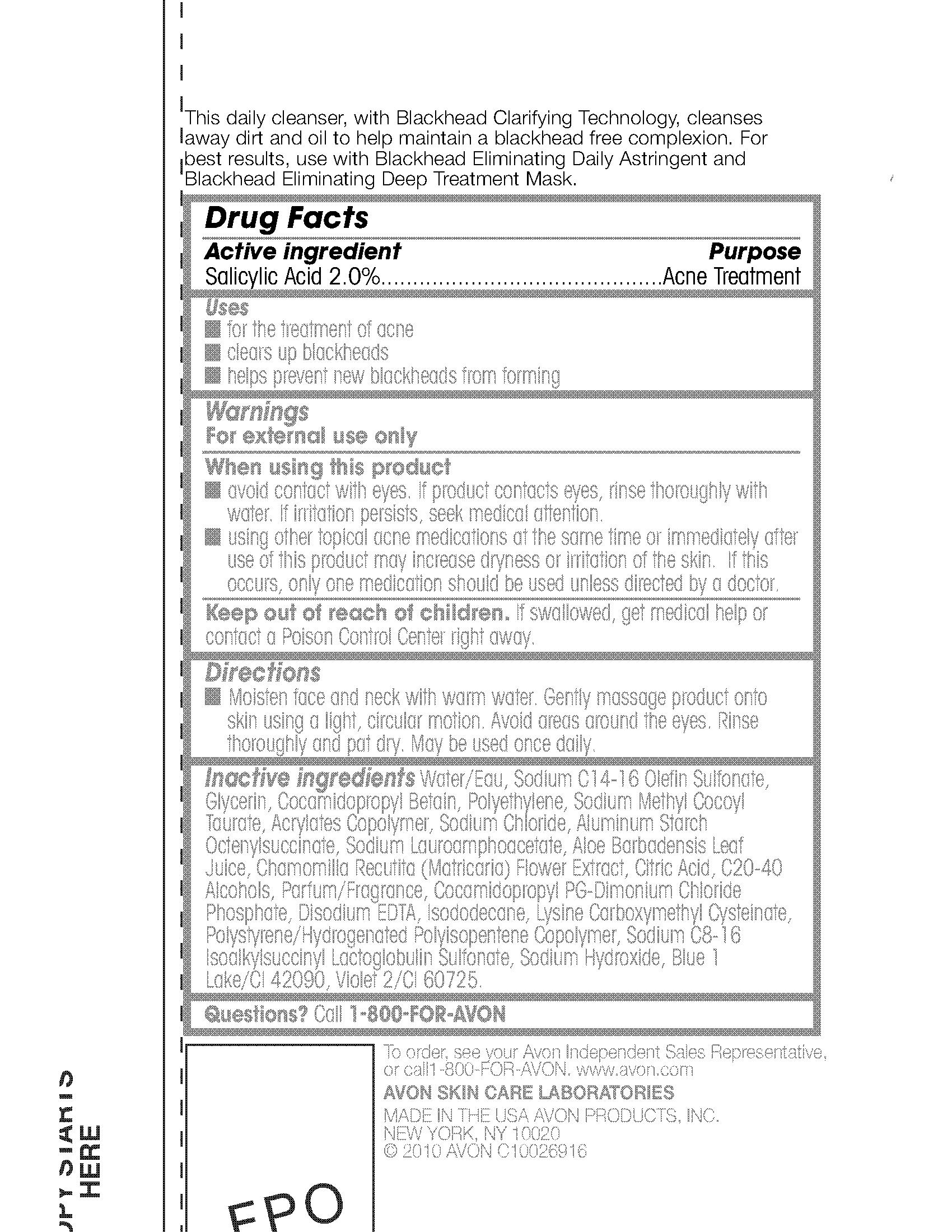 DRUG LABEL: Clearskin
NDC: 10096-0182 | Form: GEL
Manufacturer: New Avon LLC
Category: otc | Type: HUMAN OTC DRUG LABEL
Date: 20190101

ACTIVE INGREDIENTS: SALICYLIC ACID 20 mg/1 mL
INACTIVE INGREDIENTS: WATER

Clearskin Blackhead Eliminating Cleanser

Active ingredient
Salicylic Acid 2.0%..................................

Purpose

..........Acne Treatment

Uses

- for the treatment of acne
- clears up blackheads
- helps prevent new blackheads from forming

Warnings
For external use only

When using this product

- avoid contact with eyes. If product contacts eyes, rinse thoroughly with water. If irritation persists, seek medical attention.

- using other topical acne medications at the same time or immediately after use of this product may increase dryness or irritation of the skin. If this occurs, only one medication should be used unless directed by a doctor.

Keep out of reach of children. If swallowed, get medical help or
contact a Poison Control Center right away.

Directions
Moisten face and neck with warm water. Gently massage product onto
skin using a light, circular motion. Avoid areas around the eyes. Rinse
thoroughly and pat dry. May be used once daily.

INACTIVE INGREDIENT

Inactive ingredients Water/Eau, Sodium C14-16 Olefin Sulfonate,
Glycerin, Cocamidopropyl Betain, Polyethylene, Sodium Methyl Cocoyl
Taurate, Acrylates Copolymer, Sodium Chloride, Aluminum Starch
Octenylsuccinate, Sodium Lauroamphoacetate, Aloe Barbadensis Leaf
Juice, Chamomilla Recutita (Matricaria) Flower Extract, Citric Acid, C20-40
Alcohols, Parfum/Fragrance, Cocamidopropyl PG-Dimonium Chloride
Phosphate, Disodium EDTA, Isododecane, Lysine Carboxymethyl Cysteinate,
Polystyrene/Hydrogenated Polyisopentene Copolymer, Sodium C8-16
Isoalkylsuccinyl Lactoglobulin Sulfonate, Sodium Hydroxide, Blue 1
Lake/CI 42090, Violet 2/CI 60725.

Questions? Call 1-800-FOR-AVON